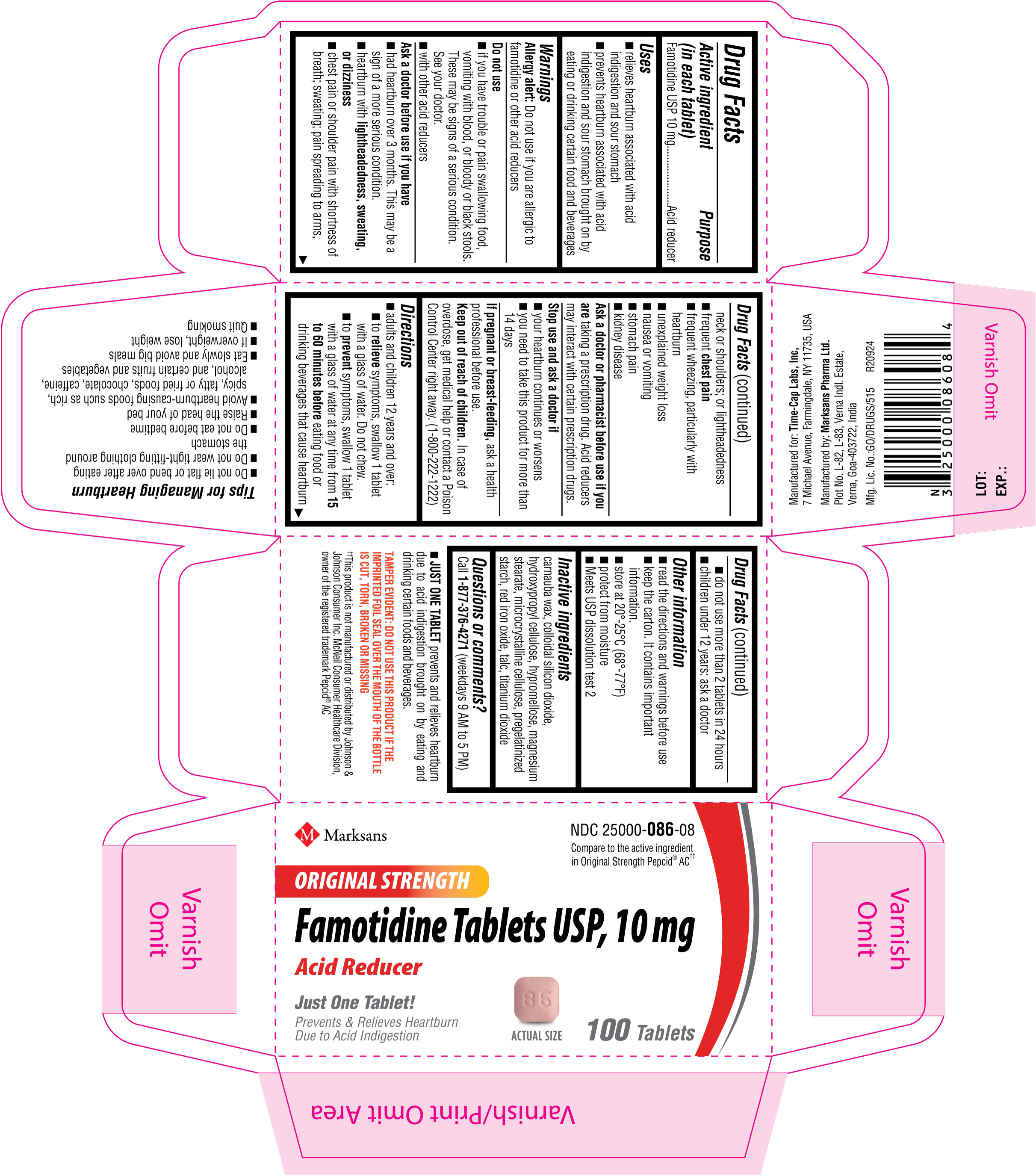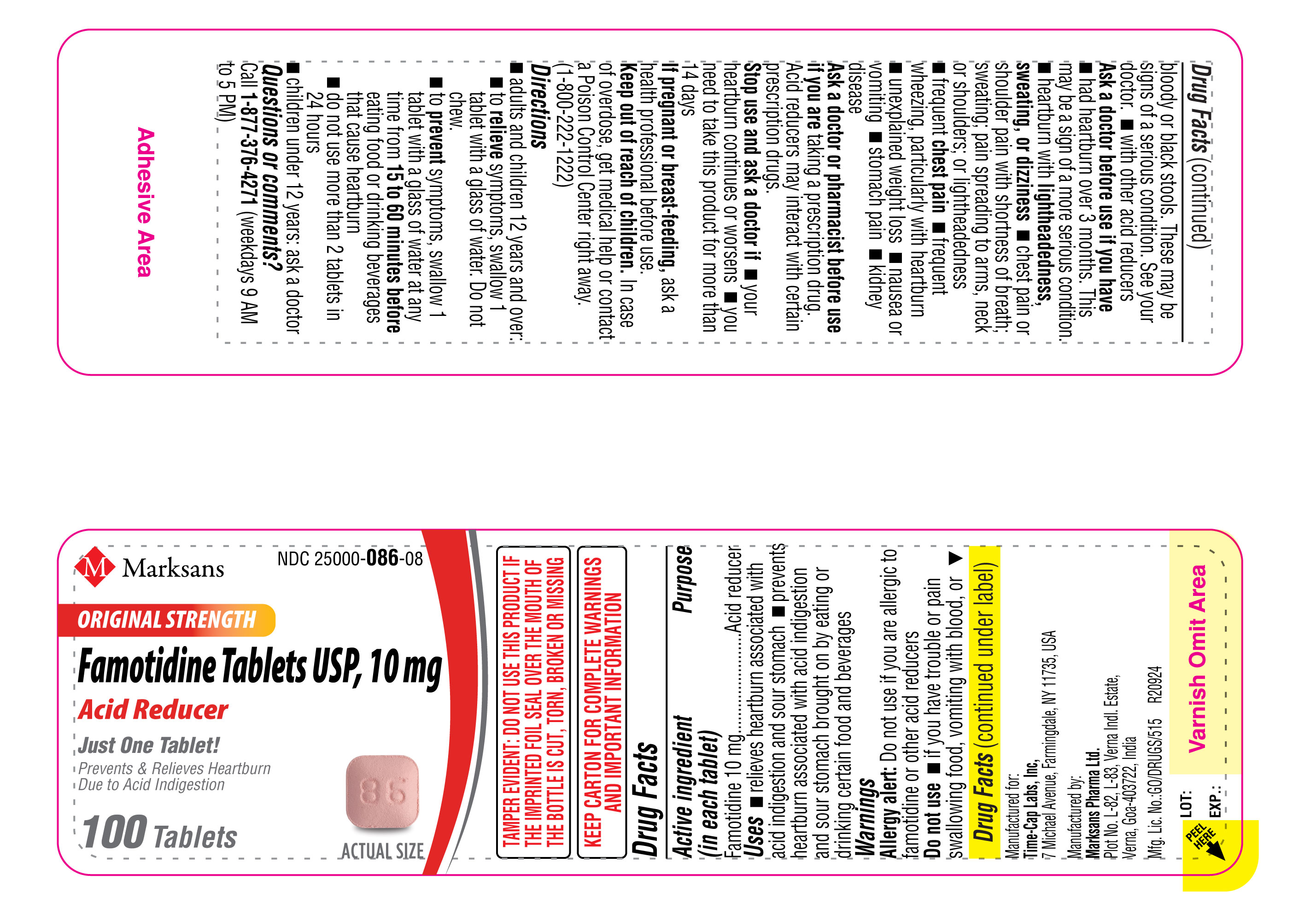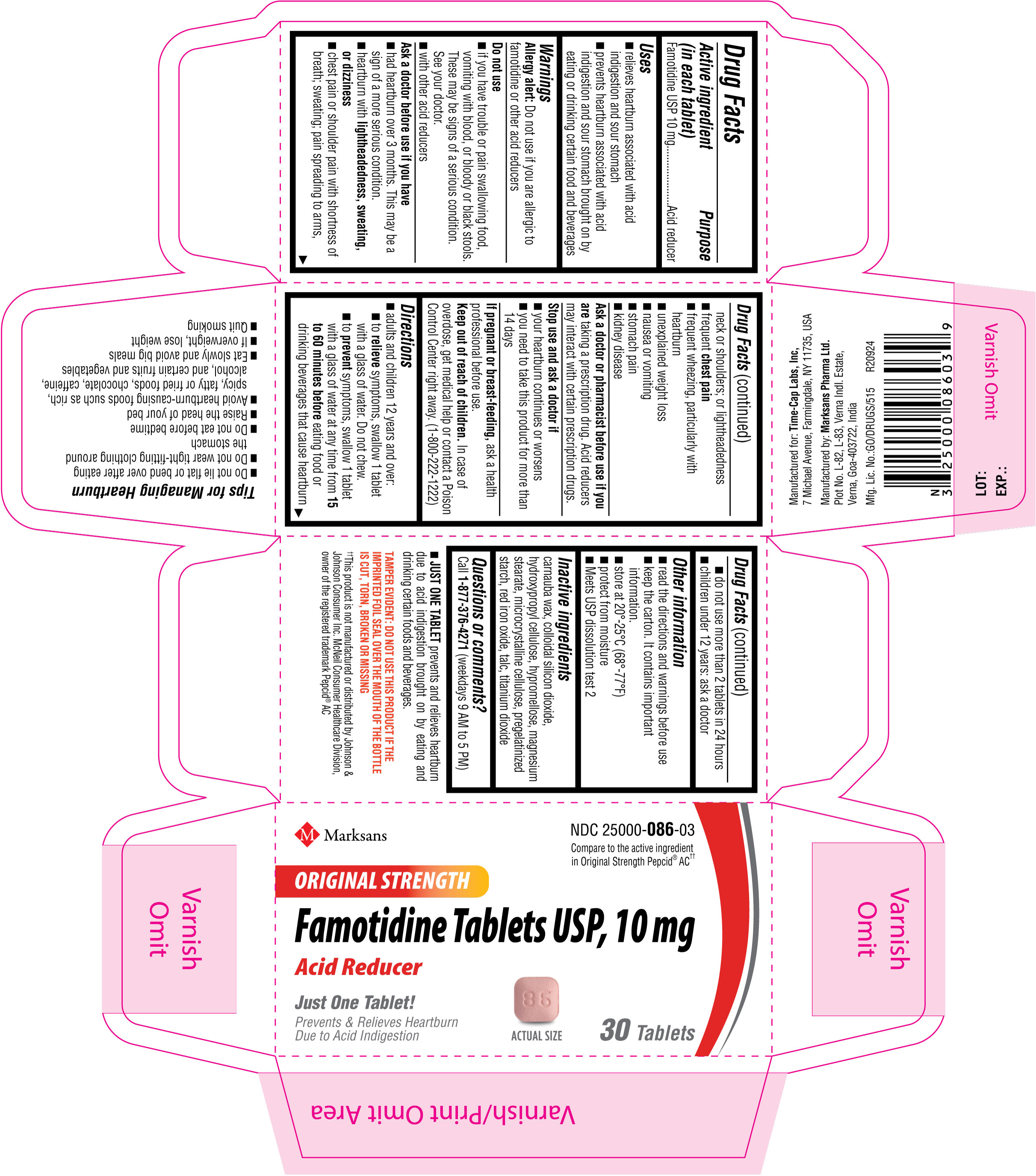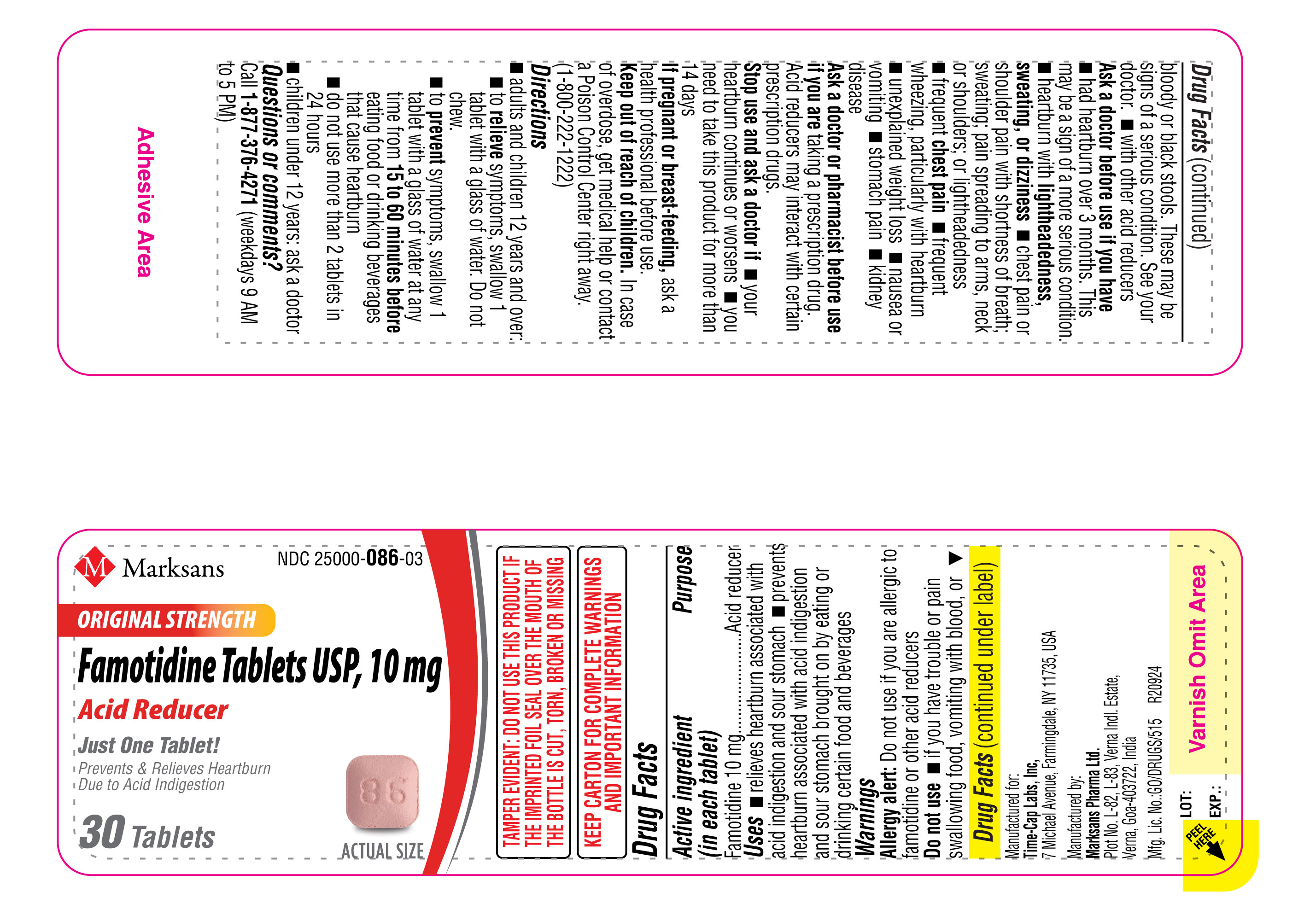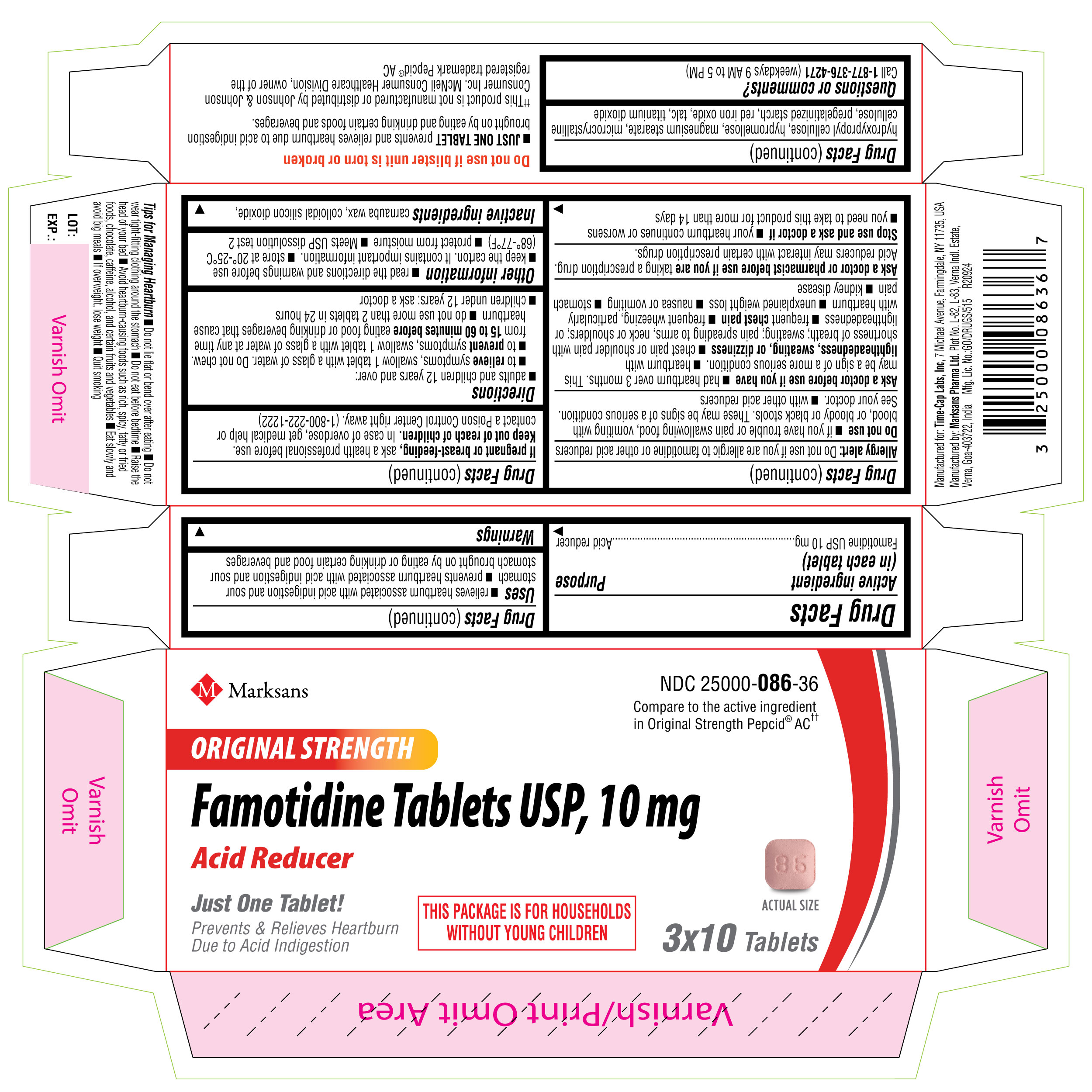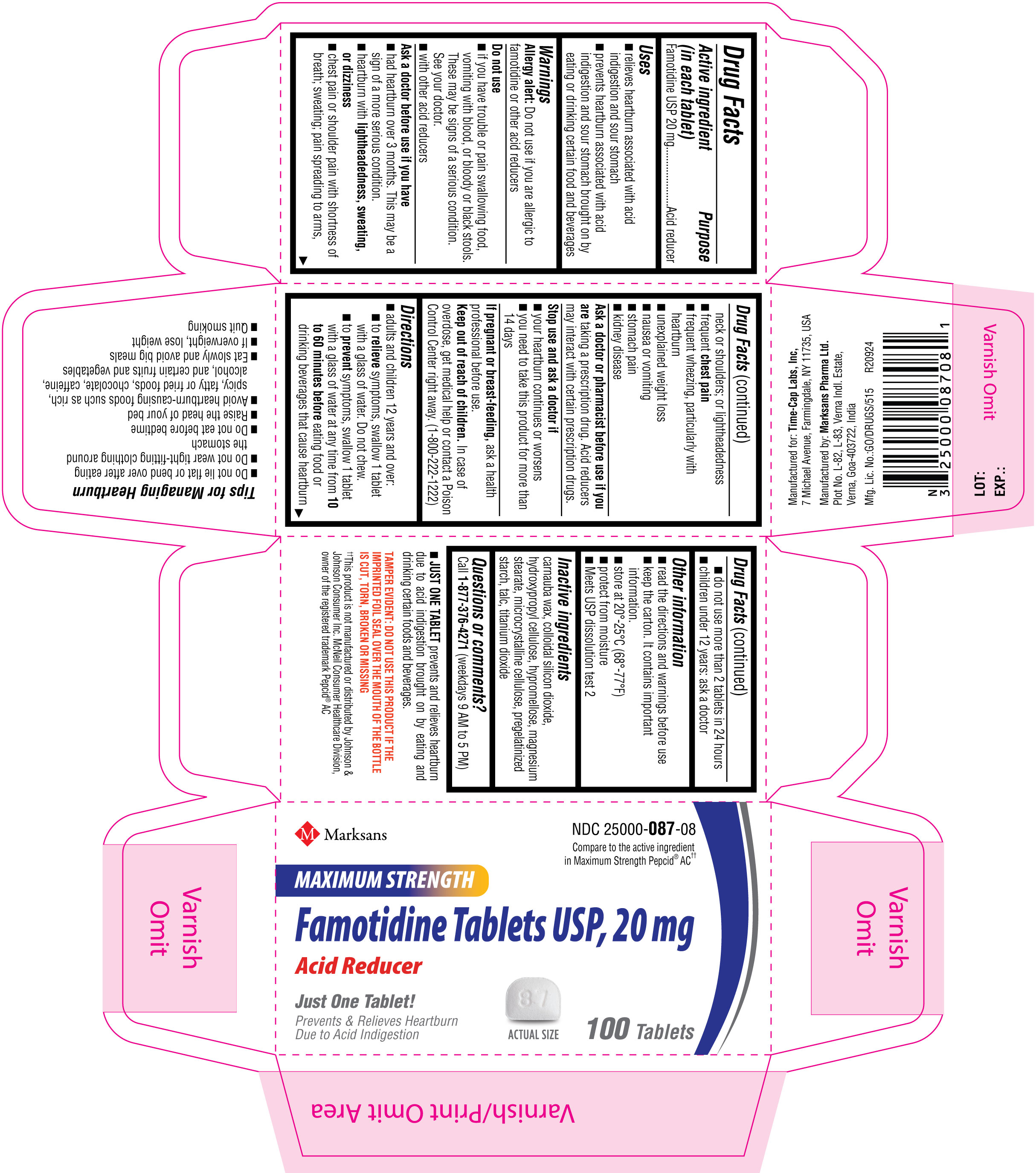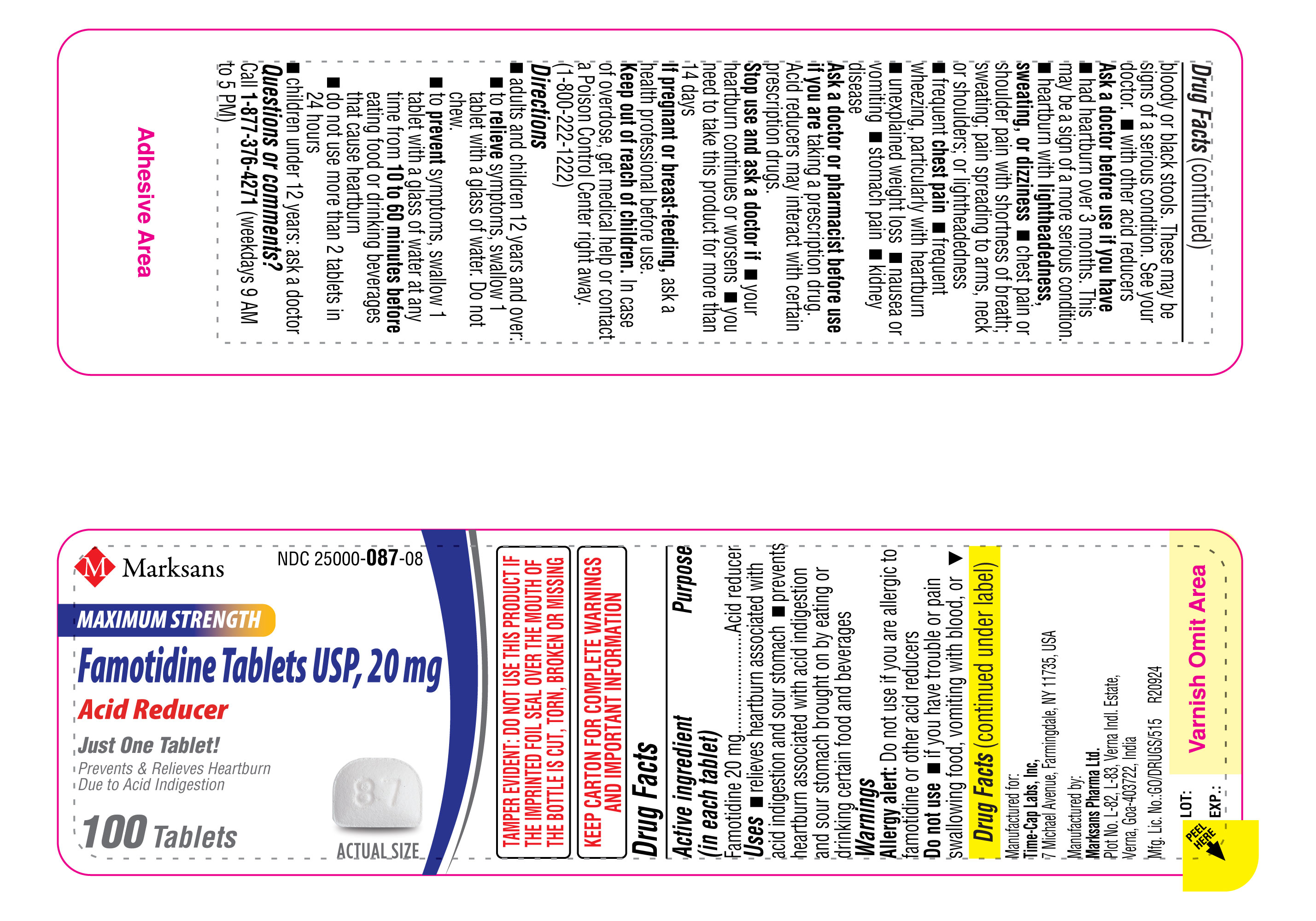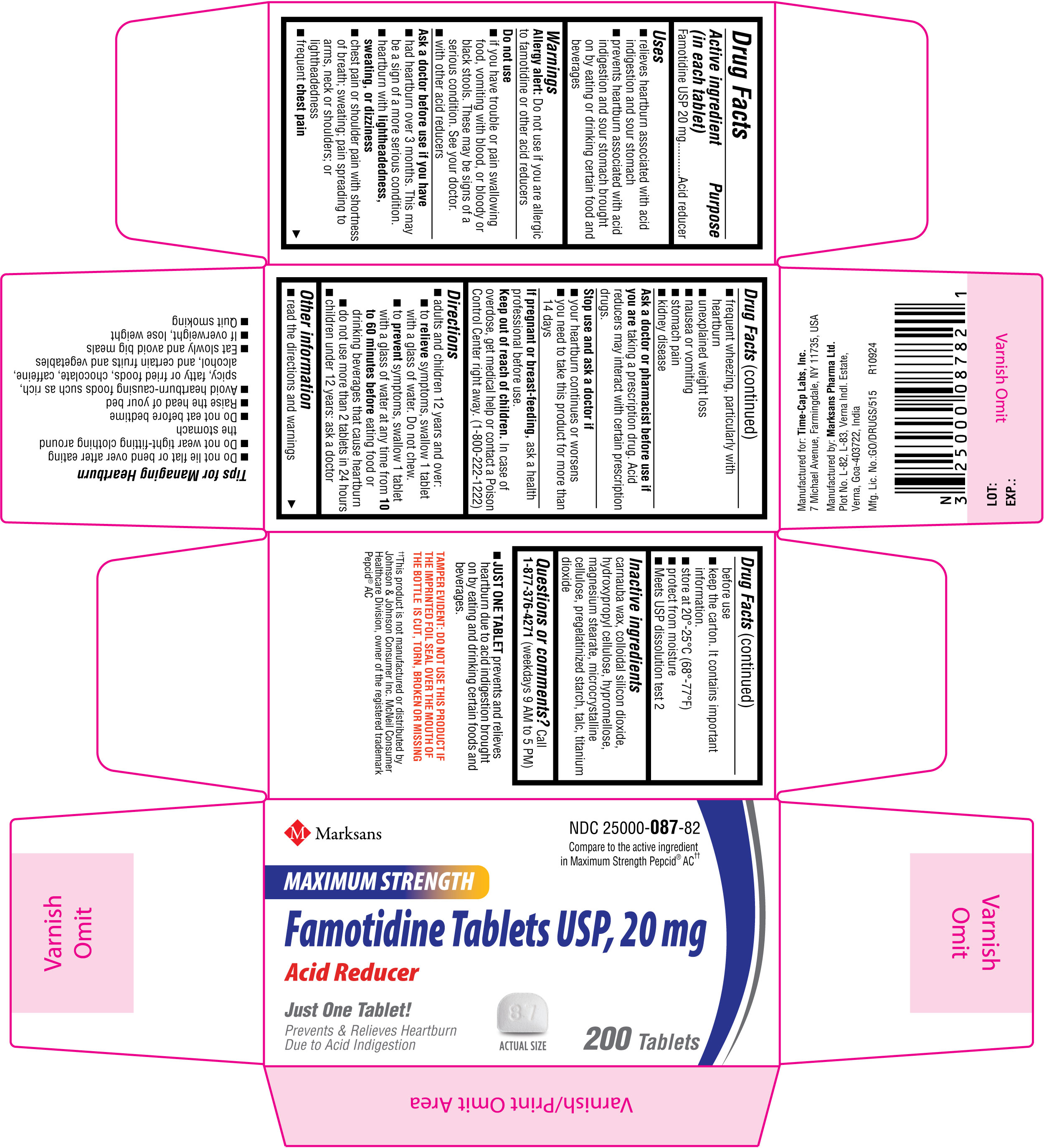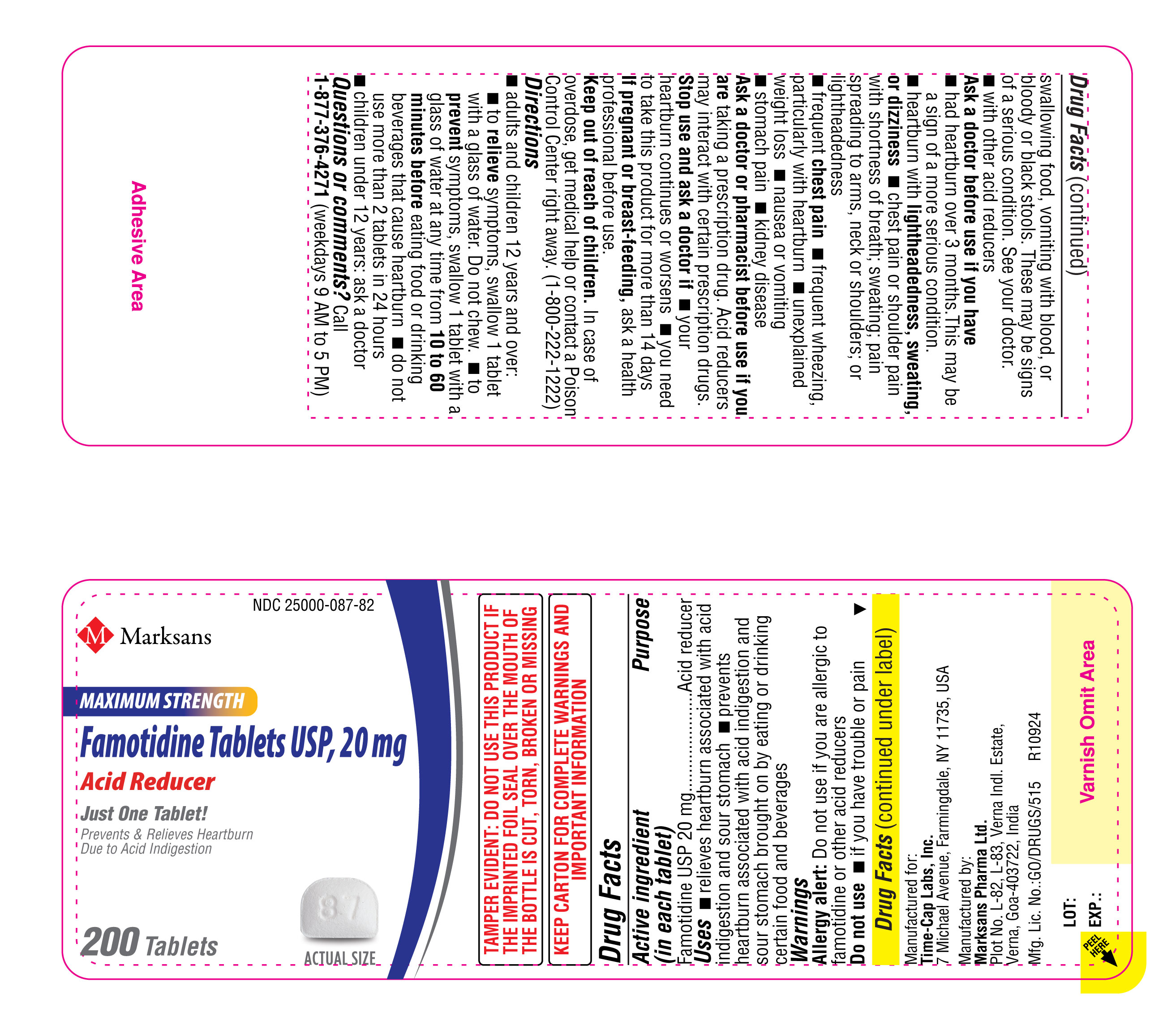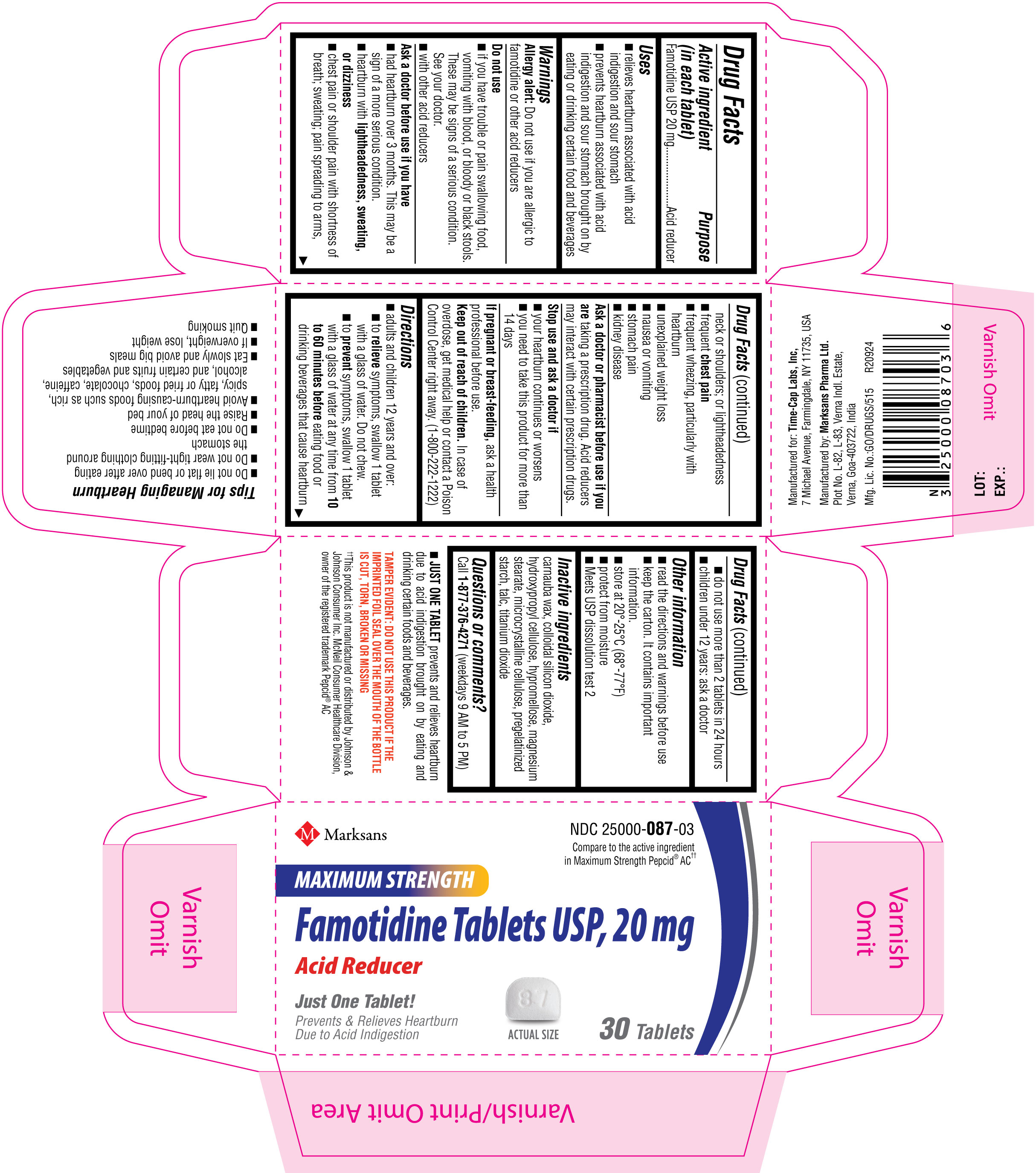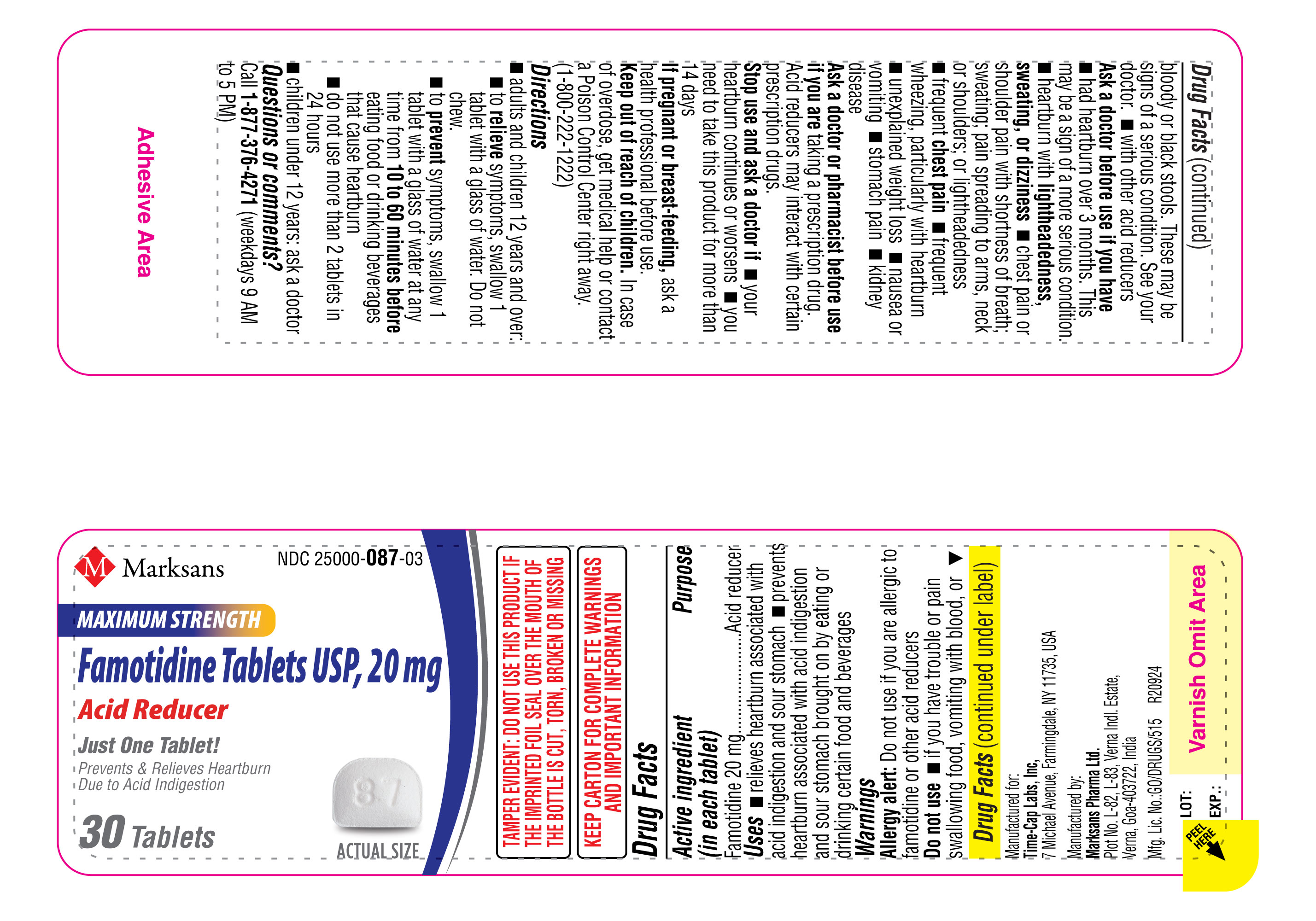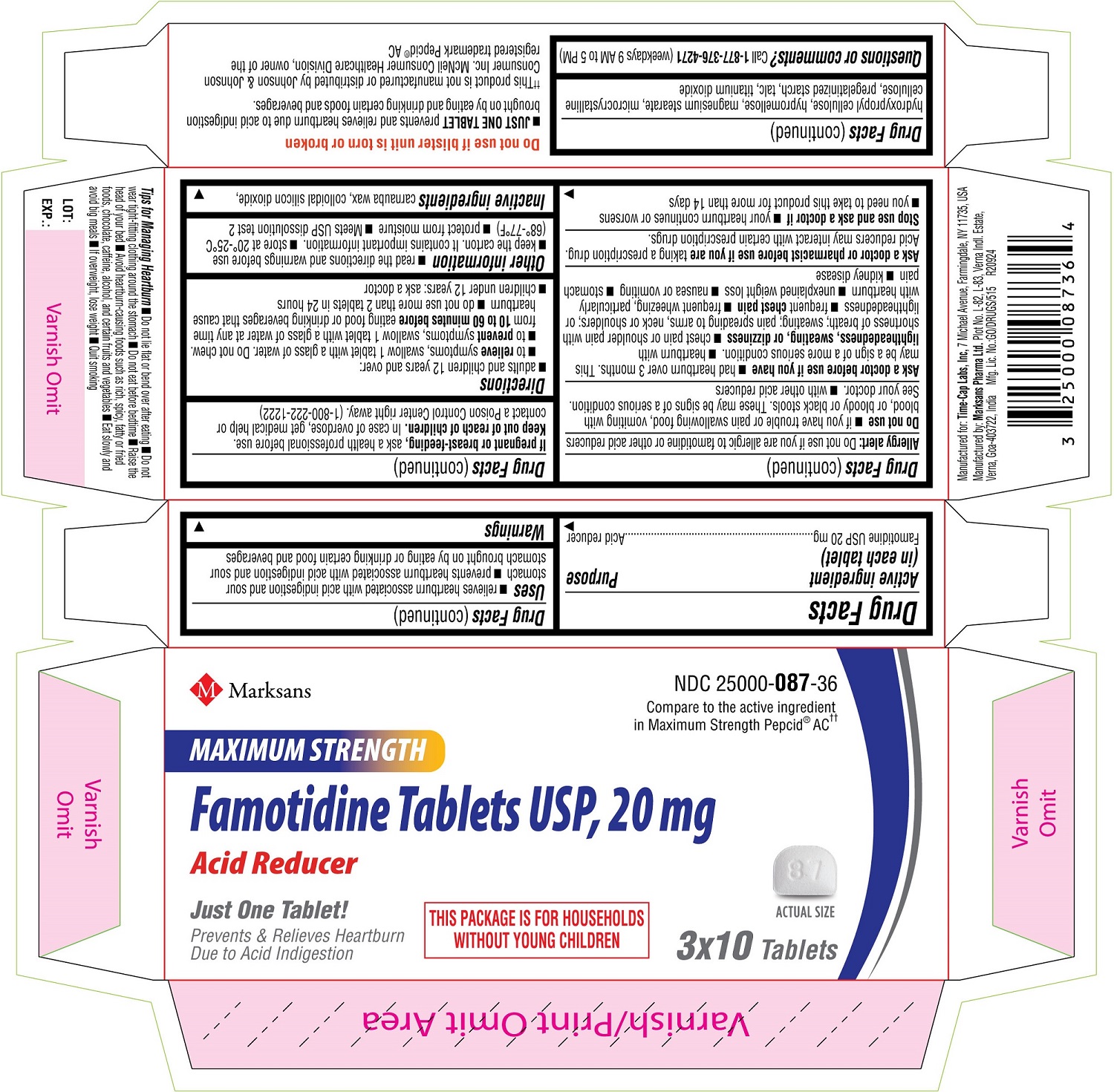 DRUG LABEL: Famotidine 10 mg
NDC: 25000-086 | Form: TABLET, COATED
Manufacturer: MARKSANS PHARMA LIMITED
Category: otc | Type: Human OTC Drug Label
Date: 20240930

ACTIVE INGREDIENTS: Famotidine 10 mg/1 1
INACTIVE INGREDIENTS: CARNAUBA WAX; SILICON DIOXIDE; HYDROXYPROPYL CELLULOSE, UNSPECIFIED; HYPROMELLOSE, UNSPECIFIED; MAGNESIUM STEARATE; MICROCRYSTALLINE CELLULOSE 102; STARCH, CORN; FERRIC OXIDE RED; TALC; TITANIUM DIOXIDE

Famotidine Tablets USP, 10 mg and 20 mg

Active ingredient (in each tablet)

For 10 mg:

Famotidine USP 10 mg

For 20 mg:

Famotidine USP 20 mg

Purpose

Acid Reducer

Uses

- relieves heartburn associated with acid indigestion and sour stomach

- prevents heartburn associated with acid indigestion and sour stomach brought on by eating or drinking certain food and beverages

Warnings

Allergy alert: Do not use if you are allergic to famotidine or other acid reducers

Do not use

• if you have trouble or pain swallowing food, vomiting with blood, or bloody or black stools. These may be signs of a serious condition. See your doctor.
• with other acid reducers

Ask a doctor before use if you have

• had heartburn over 3 months. This may be a sign of a more serious condition.
• heartburn with lightheadedness, sweating, or dizziness
• chest pain or shoulder pain with shortness of breath; sweating; pain spreading to arms, neck or shoulders; or lightheadedness
• frequent chest pain
• frequent wheezing, particularly with heartburn
• unexplained weight loss
• nausea or vomiting
• stomach pain
• kidney disease

Ask a doctor or pharmacist before use if you are

taking a prescription drug. Acid reducers may interact with certain prescription drugs.

Stop use and ask a doctor if

• your heartburn continues or worsens
• you need to take this product for more than 14 days

If pregnant or breast-feeding,

ask a health professional before use.

Keep out of reach of children.

In case of overdose, get medical help or contact a Poison Control Center right away. (1-800-222-1222)

Directions

For 10 mg:

• adults and children 12 years and over:
o to relieve symptoms, swallow 1 tablet with a glass of water. Do not chew.
o to prevent symptoms, swallow 1 tablet with a glass of water at any time from 15 to 60 minutes before eating food or drinking beverages that cause heartburn
o do not use more than 2 tablets in 24 hours
• children under 12 years: ask a doctor

For 20 mg:

• adults and children 12 years and over:
o to relieve symptoms, swallow 1 tablet with a glass of water. Do not chew.
o to prevent symptoms, swallow 1 tablet with a glass of water at any time from 10 to 60 minutes before eating food or drinking beverages that cause heartburn
o do not use more than 2 tablets in 24 hours
• children under 12 years: ask a doctor

Other information

• read the directions and warnings before use
• keep the carton. It contains important information.
• store at 20°-25°C (68°-77°F)
• protect from moisture
•Meets USP dissolution test 2

Inactive ingredients

For 10 mg:

carnauba wax, colloidal silicon dioxide, hydroxypropyl cellulose, hypromellose, magnesium stearate, microcrystalline cellulose, pregelatinized starch, red iron oxide, talc, titanium dioxide

For 20 mg:

carnauba wax, colloidal silicon dioxide, hydroxypropyl cellulose, hypromellose, magnesium stearate, microcrystalline cellulose, pregelatinized starch, talc, titanium dioxide

Questions or comments?

Call 1-877-376-4271 (weekdays 9 AM to 5 PM)

- JUST ONE TABLET prevents and relieves heartburn due to acid indigestion brought on by eating and drinking certain foods and beverages.

Tips for Managing Heartburn
• Do not lie flat or bend over after eating
• Do not wear tight-fitting clothing around the stomach
• Do not eat before bedtime
• Raise the head of your bed
• Avoid heartburn-causing foods such as rich, spicy, fatty or fried foods, chocolate, caffeine, alcohol, and certain fruits and vegetables
• Eat slowly and avoid big meals
• If overweight, lose weight
• Quit smoking

Manufactured for:
Time-Cap Labs, Inc.
7 Michael Avenue,
Farmingdale,
NY 11735, USA

Manufactured by:
Marksans Pharma Ltd.
Plot No. L-82, L-83
Verna Indl. Estate
Verna, Goa-403722, India

PRINCIPAL DISPLAY PANEL

Famotidine Tablets USP, 10 mg

NDC: 25000-086-36

Famotidine Tablets USP 10 mg

30's (3 x 10's blister) count Carton Label

NDC: 25000-086-03

Famotidine Tablets USP 10 mg

30's count Bottle Label

NDC: 25000-086-03

Famotidine Tablets USP 10 mg

30's count Carton Label

NDC: 25000-086-08

Famotidine Tablets USP 10 mg

100's count Bottle Label

NDC: 25000-086-08

Famotidine Tablets USP 10 mg

100's count Carton Label

Famotidine Tablets USP, 20 mg

NDC: 25000-087-36

Famotidine Tablets USP 20 mg

30's (3 x 10's blister) count Carton Label

NDC: 25000-087-03

Famotidine Tablets USP 20 mg

30's count Bottle Label

NDC: 25000-087-03

Famotidine Tablets USP 20 mg

30's count Carton Label

NDC: 25000-087-08

Famotidine Tablets USP 20 mg

100's count Bottle Label

NDC: 25000-087-08

Famotidine Tablets USP 20 mg

100's count Carton Label

NDC: 25000-087-82

Famotidine Tablets USP 20 mg

200's count Carton Label

NDC: 25000-087-82

Famotidine Tablets USP 20 mg

200's count Bottle Label